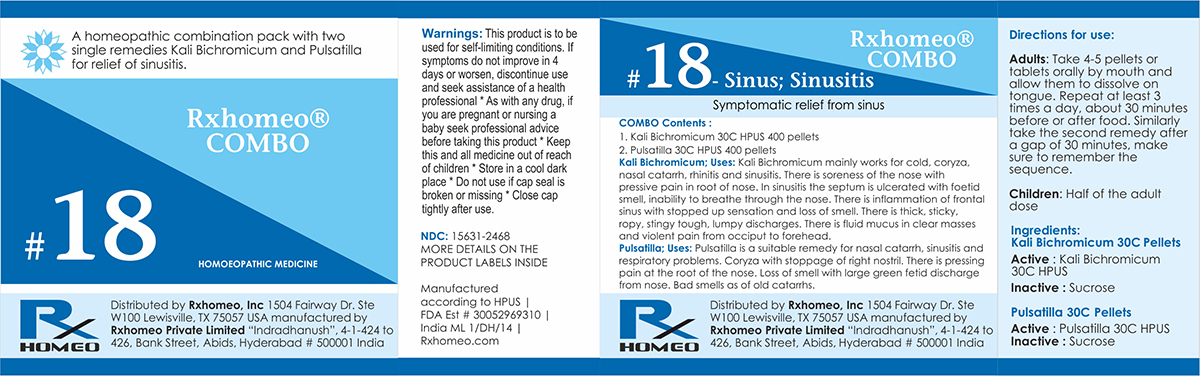 DRUG LABEL: Rxhomeo Homeopathic Combo 18
NDC: 15631-2468 | Form: KIT | Route: ORAL
Manufacturer: Rxhomeo Private Limited d.b.a.
Category: homeopathic | Type: HUMAN OTC DRUG LABEL
Date: 20161024

ACTIVE INGREDIENTS: POTASSIUM DICHROMATE 3 [hp_X]/1 1; PULSATILLA VULGARIS 1 [hp_X]/1 1
INACTIVE INGREDIENTS: SUCROSE; LACTOSE

ACTIVE INGREDIENT

KALI BICHROMICUM HPUS 3X and higher

PULSATILLA HPUS 1X and higher

USES

A homeopathic combination pack with two single remedies Kali Bichromicum and Pulsatilla for relief of sinusitis.

Kali Bichromicum: Kali Bichromicum mainly works for cold, coryza, nasal catarrh, rhinitis and sinusitis. There is soreness of the nose with pressive pain in root of nose. In sinusitis the septum is ulcerated with foetid smell, inability to breathe through the nose. There is inflammation of frontal sinus with stopped up sensation and loss of smell. There is thick, sticky, ropy, stingy tough, lumpy discharges. There is fluid mucus in clear masses and violent pain from occiput to forehead.

Pulsatilla: Pulsatilla is a suitable remedy for nasal catarrh, sinusitis and respiratory problems. Coryza with stoppage of right nostril. There is pressing pain at the root of the nose. Loss of smell with large green fetid discharge from nose. Bad smells as of old catarrhs.

INDICATIONS

Condition listed above or as directed by the physician

DOSAGE

Adults: Take 4-5 pellets or tablets orally by mouth and allow them to dissolve on tongue. Repeat at least 3 times a day, about 30 minutes before or after food. Similarly take the second remedy after a gap of 30 minutes, make sure to remember the sequence.

Children: Half of the adult dose.

WARNINGS

This product is to be used for self-limiting conditions

STOP USE

If symptoms do not improve in 4 days, or worsen, discontinue use and seek assistance of health professional

KEEP OUT OF REACH OF CHILDREN

Keep this and all medication out of reach of children

Do not use if capseal is broken or missing.

Close the cap tightly after use.

INACTIVE INGREDIENTS

Sucrose for Pellets.

Lactose for Tablets.

STORAGE

Store in a cool dark place

QUESTIONS OR COMMENTS

www.Rxhomeo.com | 1.888.2796642 | info@rxhomeo.com
Rxhomeo, Inc 1504 Fairway Dr. Ste W 100 Lewisville, TX 75057 USA